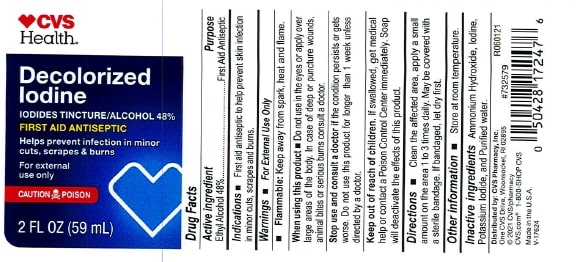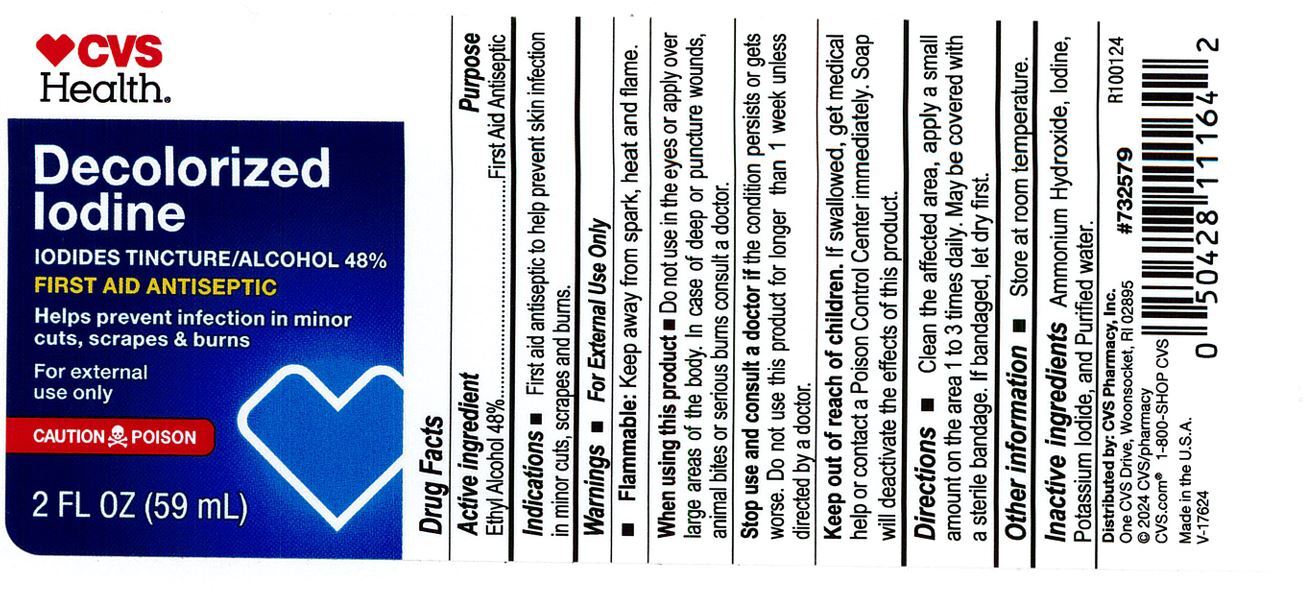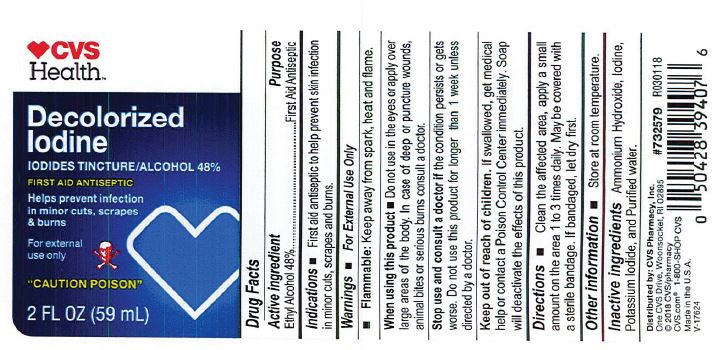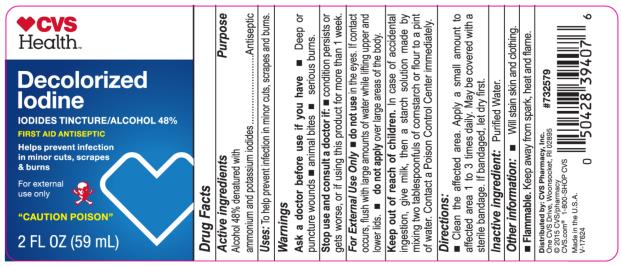 DRUG LABEL: CVS Decolorized Iodine
NDC: 69842-207 | Form: LIQUID
Manufacturer: CVS Pharmacy
Category: otc | Type: HUMAN OTC DRUG LABEL
Date: 20241218

ACTIVE INGREDIENTS: ALCOHOL 0.48 mL/1 mL
INACTIVE INGREDIENTS: AMMONIA; IODINE; POTASSIUM IODIDE; WATER

CVS Decolorized Iodine

CVS Decolorized Iodine

Drug Facts

Active Ingredient

Alcohol 48%

Purpose

Antiseptic

Uses

To help prevent infection in in minor: cuts, scrapes and burns.

Warnings

Ask a doctor before use if you have

deep or puncture wounds. Animal bites. Serious burns.

Stop use and consult a doctor if

Condition persists or gets worse, or if using this product for more than 1 week.

For external use only. Do not use in the eyes. If contact occurs, flush with large amounts of water while lifting upper and lower lids. Do not apply over large areas of the body.

Keep out of reach of children.

- In case of accidental ingestion, give milk, then a starch solution made by mixing two tablespoonfuls of cornstarch or flour to a pint of water, Contact a Poison Control Center immediately.

Directions

- Clean the affected area. Apply a small amount to the affected area 1 to 3 times daily. May be covered with a sterile bandage. If bandaged, let dry first.

Inactive Ingredient

Ammonia, iodine, potassium iodide, purified water.

Other information

Will stain skin and clothing

Flammable

Keep away from spark, heat and flame

PRINCIPAL DISPLAY PANEL

Decolorized
Iodine
First Aid Antiseptic
2 FL OZ (59 mL)